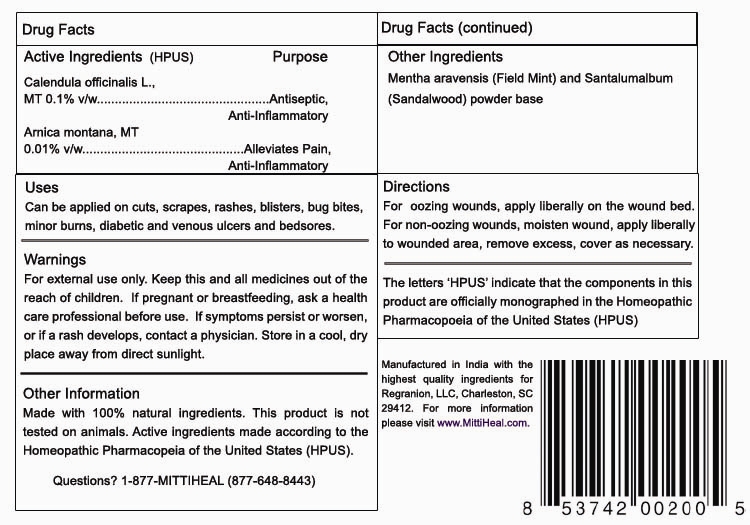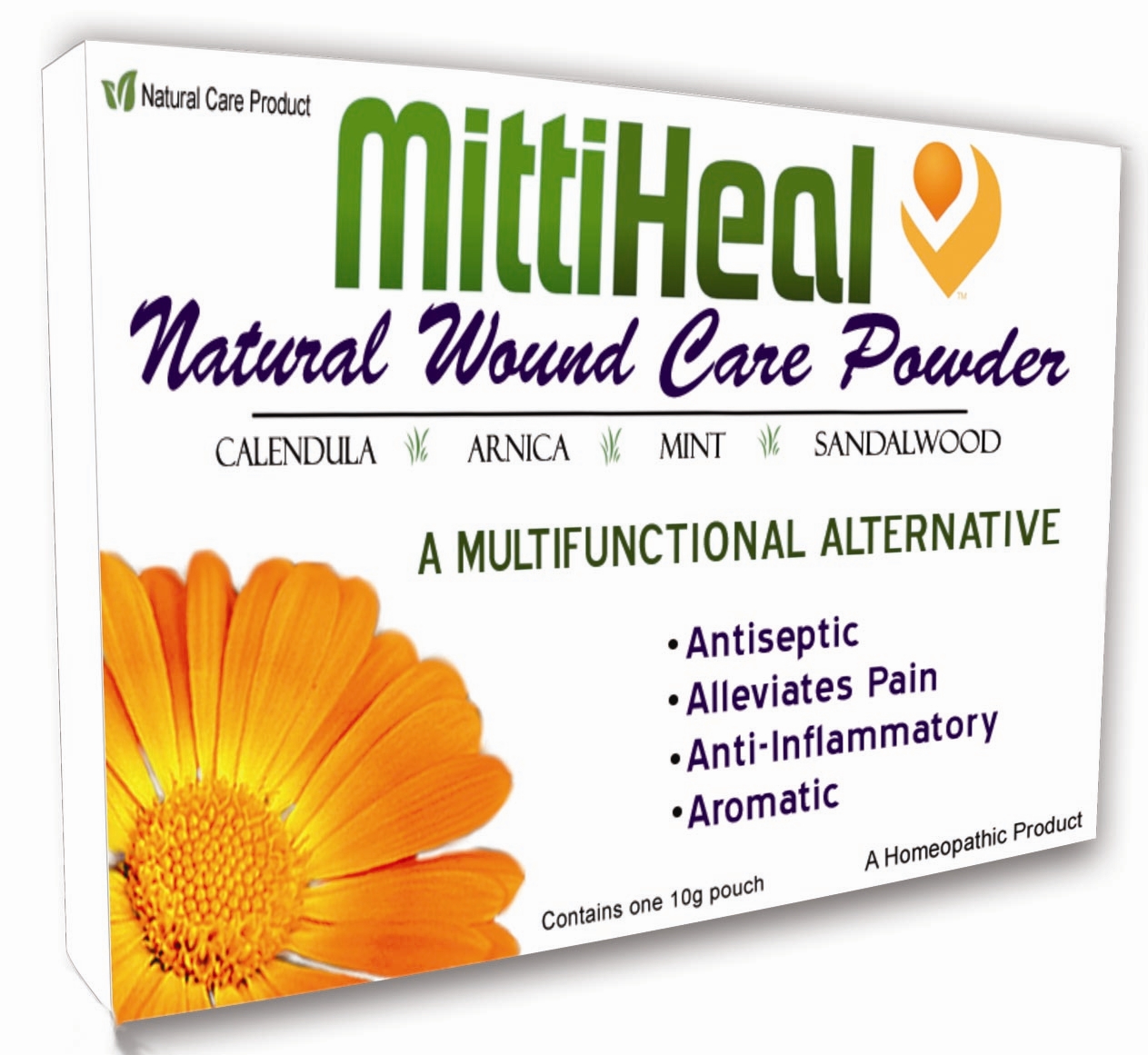 DRUG LABEL: MittiHeal
NDC: 51720-734 | Form: POWDER
Manufacturer: Curative Power Lab PVT LTD
Category: homeopathic | Type: HUMAN OTC DRUG LABEL
Date: 20101029

ACTIVE INGREDIENTS: CALENDULA OFFICINALIS FLOWERING TOP 6 [hp_X]/10 g; ARNICA MONTANA 6 [hp_X]/10 g
INACTIVE INGREDIENTS: MINT 9 g/10 g; SANDALWOOD 1 g/10 g

MittiHeal

Active Ingredients Purpose

Calendula Officinalis L., MT 0.1% v/w......................Antiseptic, Anti-Inflammatory

Arnica Montana, MT 0.01% v/w...............................Alleviates Pain, Anti-Inflammatory

INACTIVE INGREDIENT

Mentha arvensis (Field Mint) and Santalum album (Sandalwood) powder base

PURPOSE

Mittiheal. A multi-functional alternative.
- Antiseptic
- Anti-itch
- Alleviates Pain
- Aromatic

INDICATIONS AND USAGE

Can be applied on cuts, scrapes, rashes, blisters, bug bites, minor burns, diabetic and venous ulcers, and bedsores. Calms skin and provides itch relief.

DOSAGE AND ADMINISTRATION

For oozing wounds, apply liberally on the wound bed. The powder will absorb fluids from the wound and form a crust. For non-oozing wounds, moisten wound, apply liberally to wounded area, remove excess, cover, and reapply as necessary.

For best results, use within 90 days of opening.

WARNINGS

For external use only. If pregnant or breastfeeding, ask a health care professional before use. If symptoms persist or worsen, or if a rash develops, contact a physician. Store in a cool, dry place away from direct sunlight.

Keep out of the reach of children.

HOW SUPPLIED

Manufactured in India with the highest quality ingredients for Regranion, LLC, Charleston, SC 29403. For more information please visit www.mittiheal.com

REFERENCES

Made with 100% natural ingredients. Active ingredients made according to the Homeopathic Pharmacopoeia of the United States (HPUS).

The letters 'HPUS' indicate that the components in this product are officially monographed in the Homeopathic Pharmacopoeia of the United States (HPUS).

Questions? 1-877-MITTIHEAL (877-648-8443)

www.mittiheal.com